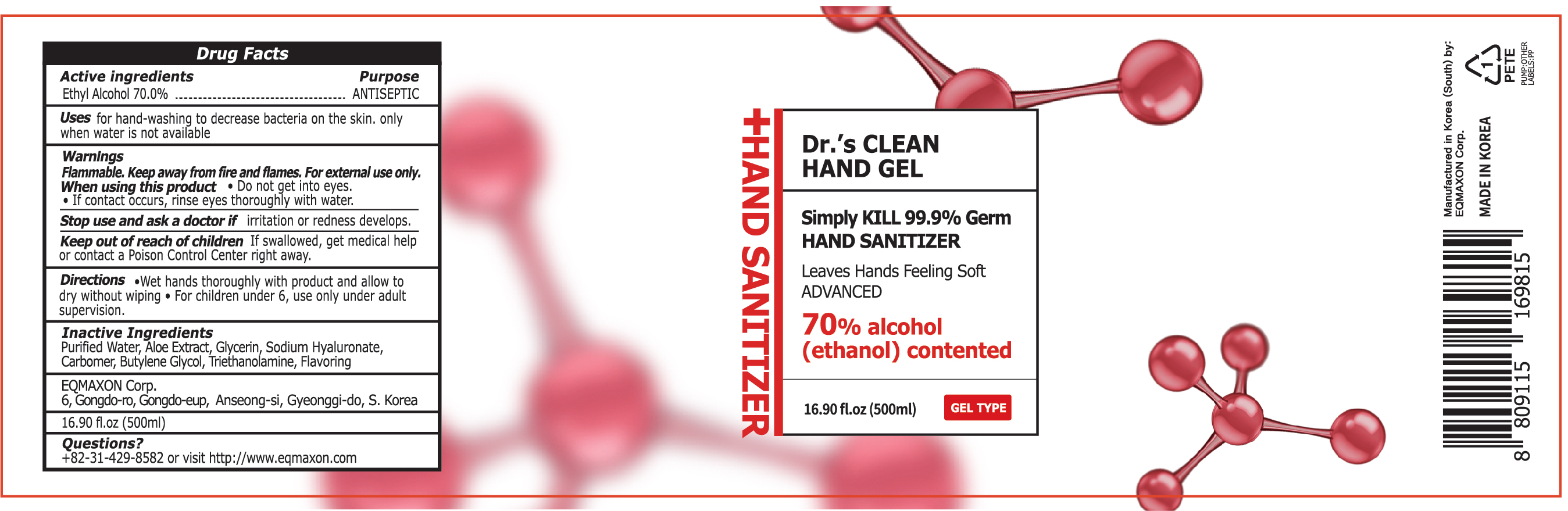 DRUG LABEL: Dr.s Clean Hand
NDC: 55526-0011 | Form: GEL
Manufacturer: EQMAXON Corp
Category: otc | Type: HUMAN OTC DRUG LABEL
Date: 20200418

ACTIVE INGREDIENTS: ALCOHOL 70 mL/100 mL
INACTIVE INGREDIENTS: Water; ALOE; Glycerin; HYALURONATE SODIUM; CARBOMER HOMOPOLYMER, UNSPECIFIED TYPE; Butylene Glycol; TROLAMINE

ACTIVE INGREDIENT

Active ingredients: Ethyl Alcohol 70.0%

INACTIVE INGREDIENT

Inactive ingredients:

Purified Water, Aloe Extract, Glycerin, Sodium Hyaluronate, Carbomer, Butylene Glycol, Triethanolamine, Flavor

PURPOSE

Purpose: ANTISEPTIC

WARNINGS

Flammable. Keep away from fire and flames. For external use only.

When using this product • Do not get into eyes. • If contact occurs, rinse eyes thoroughly with water.

Stop use and ask a doctor if irritation or redness develops.

Keep out of reach of children. If swallowed, get medical help or contact a Poison Control Center right away

Keep out of reach of children. If swallowed, get medical help or contact a Poison Control Center right away

Uses

for hand-washing to decrease bacteria on the skin, only when water is not available

Directions

Wet hands thoroughly with product and allow to dry without wiping

For children under 6, use only under adult supervision.